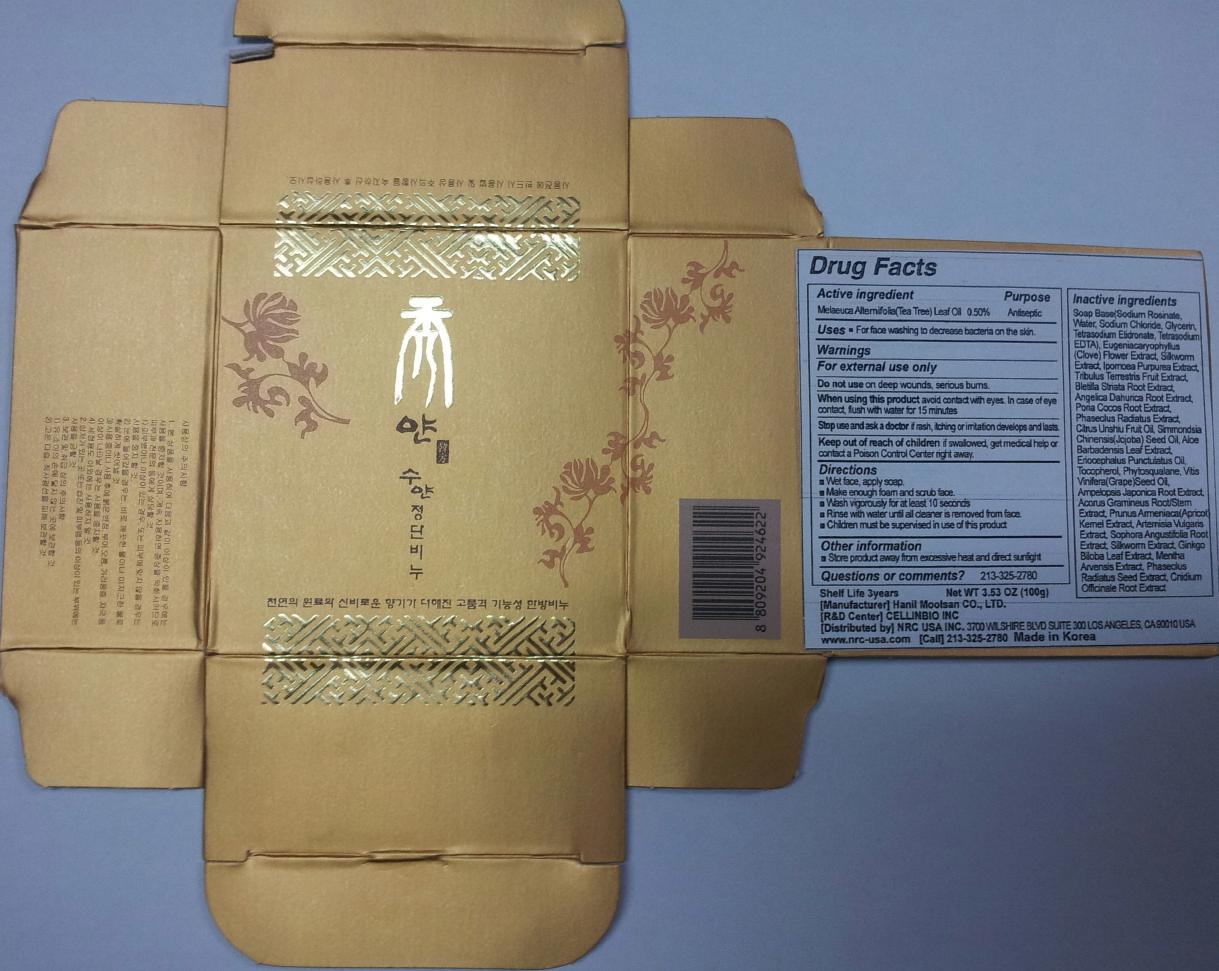 DRUG LABEL: SUYAN JEONGDAN
NDC: 76173-1008 | Form: SOAP
Manufacturer: Cellinbio Co Ltd
Category: otc | Type: HUMAN OTC DRUG LABEL
Date: 20111212

ACTIVE INGREDIENTS: TEA TREE OIL 0.5 g/100 g
INACTIVE INGREDIENTS: WATER; SODIUM CHLORIDE; GLYCERIN; EDETATE SODIUM; CLOVE; IPOMOEA PURPUREA TOP; TRIBULUS TERRESTRIS FRUIT; BLETILLA STRIATA BULB; ANGELICA DAHURICA ROOT; CITRUS RETICULATA FRUIT OIL; JOJOBA OIL; ALOE VERA LEAF; TOCOPHEROL; GRAPE SEED OIL; AMPELOPSIS JAPONICA ROOT; ACORUS GRAMINEUS ROOT; PRUNUS ARMENIACA SEED; ARTEMISIA PRINCEPS LEAF; SOPHORA FLAVESCENS ROOT; GINKGO; MUNG BEAN; CNIDIUM OFFICINALE ROOT

SUYAN JEONGDAN

drug facts

Active ingredient
Melaeuca Alternifolia(Tea Tree) Leaf Oil 0.50%

Purpose

Antiseptic

Keep out of Reach of Children

if swallowed, get medical help or contact a Poison Control Center right away

Indication & Usage

Directions
■ Wet face, apply soap.
■ Make enough foam and scrub face.
■ Wash vigorously for at least 10 seconds
■ Rinse with water until all cleaner is removed from face.
■ Children must be supervised in use of this product

Warnings

For external use only.
Do not use on Deep wounds, serious burns.
When using this product avoid contact with eyes. In case of eye contact, flush with water for 15 minutes.
Stop use and ask a doctor if rash, itching or irritation develops and lasts.

Dosage & Administration

For face washing to decrease bacteria on the skin.

Inactive Ingredient

Soap Base(Sodium Rosinate, Water, Sodium Chloride, Glycerin, Terasodim Etidronate, Tetrasodim EDTA), Eugeniacaryophyllus(Clove) Flower Extract, Silkworm Extract, Ipomoea Purpurea Extract, Tribulus Terrestris Fruit Extract, Bletilla Striata Root Extract, Angelica Dahurica Root Extract, Poria Cocos Root extract, Phaseolus Radiatus Extract, Unshiu oil, Simmondsia Chinensis(Jojoba) Seed Oil, Aloe Barbadensis Leaf Extract, Eriocephalus Punctulatus Oil, Tocopherol, Phytosqualane, Vitis Vinifera(Grape)Seed Oil, Ampelopsis japonica Root Extract, Acorus Gramineus Root/Stem Extract, Prunus Armeniaca(Apricot)Kernel Extract, Artemisia Vulgaris Extract, Sophora Angustifolia root Extract, Silkworm Extract, Ginkgo biloba Leaf Extract, Mentha Arvensis Extract, Phaseolus radiatus Seed Extract Vigna Radiata Seed Extract, Cnidium Officinale Root Extract

SUYAN JEONGDAN

SUYAN JEONGDAN SOAP
Net WT. 3.53 OZ (100g)